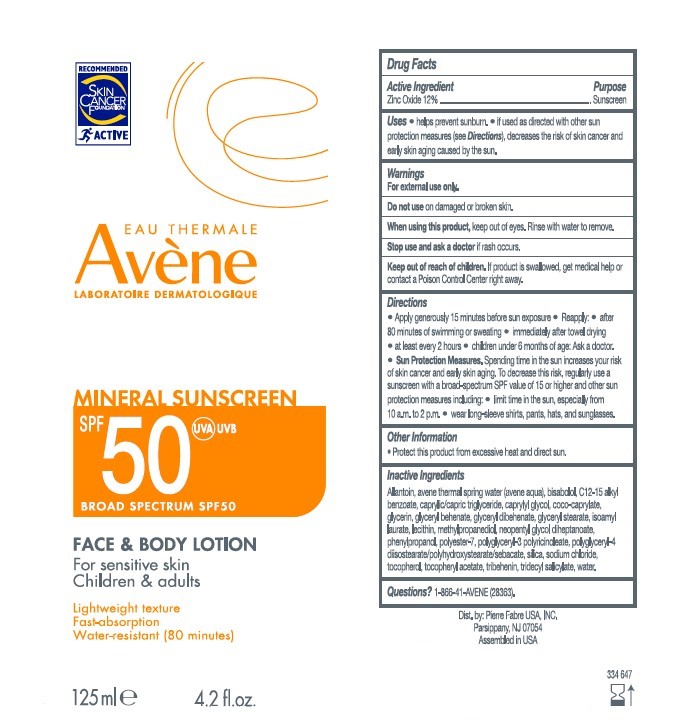 DRUG LABEL: Avene Mineral Sunscreen Face and Body
NDC: 64760-780 | Form: LOTION
Manufacturer: Pierre Fabre USA Inc.
Category: otc | Type: HUMAN OTC DRUG LABEL
Date: 20241106

ACTIVE INGREDIENTS: ZINC OXIDE 120 mg/120 mg
INACTIVE INGREDIENTS: ISOAMYL LAURATE; COCO-CAPRYLATE; CAPRYLIC/CAPRIC/LAURIC TRIGLYCERIDE; ALKYL (C12-15) BENZOATE; TRIDECYL SALICYLATE; GLYCERYL DIBEHENATE; ALLANTOIN; .ALPHA.-TOCOPHEROL ACETATE; POLYGLYCERYL-3 PENTARICINOLEATE; GLYCERYL STEARATE SE; POLYESTER-7; NEOPENTYL GLYCOL DIHEPTANOATE; GLYCERYL BEHENATE/EICOSADIOATE; PHENYLPROPANOL; TOCOPHEROL; GLYCERIN; SODIUM CHLORIDE; POLYGLYCERYL-4 DIISOSTEARATE/POLYHYDROXYSTEARATE/SEBACATE; METHYLPROPANEDIOL; CAPRYLYL GLYCOL; LEVOMENOL; LECITHIN, SOYBEAN; WATER; SILICON DIOXIDE; TRIBEHENIN

Avene Mineral Sunscreen Face & Body Lotion SPF 50

Purpose

Sunscreen

Active Ingredient

Zinc Oxide 12%

Uses

helps prevent sunburn.

if used as directed with other sun protection measures (see Directions), decreased the risk of skin cancer and early skin aging caused by the sun.

Warnings

For external use only.

Do not use

on damaged or broken skin.

When using this product

keep out of eyes. Rinse with water to remove.

Stop use and ask a doctor

if rash occurs.

Keep out of reach of children.

If product is swallowed, get medical help or contact a Poison Control Center right away.

Directions

Apply generously 15 minutes before sun exposure.

Reapply:

- after 80 minutes of swimming or sweating.
- immediately after towel drying.
- at least every 2 hours.
- children under 6 months of age: Ask a doctor.

Sun Protection Measures. Spending time in te sun increases your risk of skin cancer and early skin aging. To decrease this risk, regularly use a sunscreen with a broad-spectrum SPF value of 15 or higher and other sun protection measures including:

- limit time in the sun, especially from 10 a.m. to 2 p.m.
- wear long-sleeve shirts, pants, hats, and sunglasses.

Other Information

Protect this product from excessive heat and direct sun.

Inactive Ingredients

Allantoin, avene thermal spring water (avene aqua), bisabolol, C12-C15 alkyl benzoate, caprylic/capric triglyceride, caprylyl glycol, coco-caprylate, glycerin, glyceryl behenate, glyceryl dibehenate, glyceryl stearate, isoamyl laurate, lecithin, methylpropanediol, neopentyl glycol diheptanoate, phenylpropanol, polyester-7, polyglyceryl-3 polricinoleate, polyglyceryl-4 diisostearate/polyhydroxystearate/sebacate, silica, sodium chloride, tocopherol, tocopheryl acetate, tribehenin, tridecyl salic

Questions?

1-866-41-AVENE (28363)

Package Label

EAU THERMALE

AVENE

LABORATORIE DERMATOLOGIQUE

MINERAL SUNSCREEN

SPRF 50 UVA-UVB

BROAD SPECTRUM SPF50

FACE & BODY LOTION

FOR SENSITIVE SKIN

CHILDREN & ADULTS

LIGHTWEIGHT TEXTURE

FAST-ABSORPTION

WATER-RESISTANT (80 MINUTES)

125ML 4.2 FL.OZ.